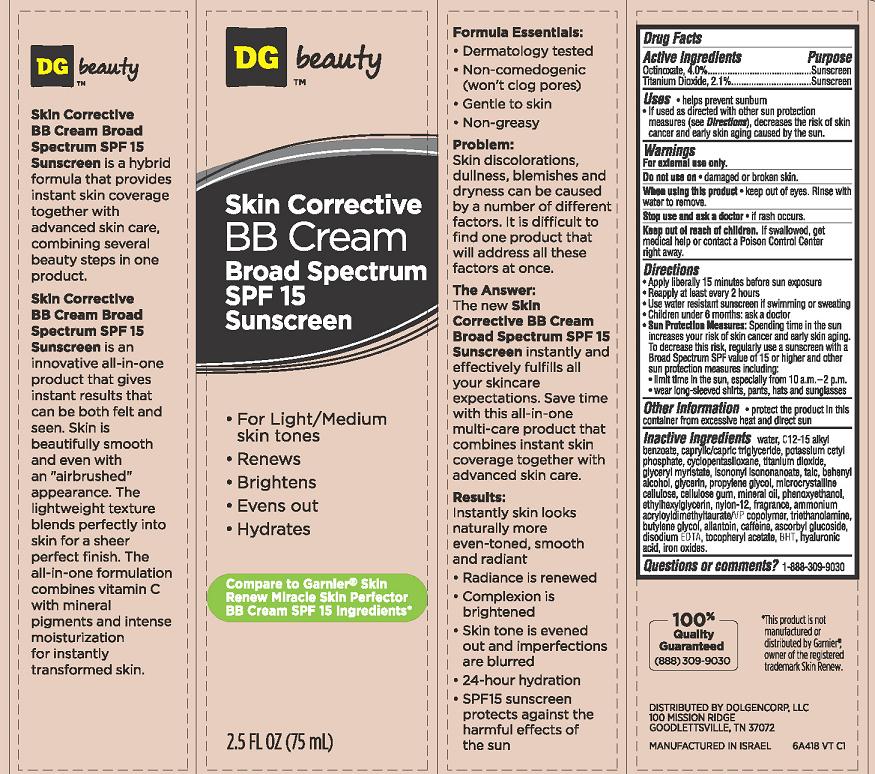 DRUG LABEL: Skin Corrective BB Cream Broad Spectrum SPF15 Sunscreen
NDC: 55910-418 | Form: CREAM
Manufacturer: Dolgencorp Inc.
Category: otc | Type: HUMAN OTC DRUG LABEL
Date: 20130715

ACTIVE INGREDIENTS: TITANIUM DIOXIDE 2.1 g/100 mL; OCTINOXATE 4 g/100 mL
INACTIVE INGREDIENTS: WATER; ALKYL (C12-15) BENZOATE; TRICAPRIN; POTASSIUM CETYL PHOSPHATE; CYCLOMETHICONE 5; GLYCERYL MYRISTATE; ISONONYL ISONONANOATE; DOCOSANOL; MINERAL OIL; TALC; GLYCERIN; PROPYLENE GLYCOL; CELLULOSE, MICROCRYSTALLINE; CARBOXYMETHYLCELLULOSE SODIUM; PHENOXYETHANOL; ETHYLHEXYLGLYCERIN; FERROUS OXIDE; NYLON-12; TROLAMINE; AMMONIUM ACRYLOYLDIMETHYLTAURATE/VP COPOLYMER; BUTYLENE GLYCOL; ALLANTOIN; CAFFEINE; ASCORBIC ACID; EDETATE DISODIUM; .ALPHA.-TOCOPHEROL ACETATE; BUTYLATED HYDROXYTOLUENE; HYALURONIC ACID

DG™ beauty Skin Corrective BB Cream Broad Spectrum SPF15 Sunscreen

Active ingredient

Octinoxate 4.0%
Titanium Dioxide 2.1%

Purpose

Sunscreen

Uses

- helps prevent sunburn
- If used as directed with other sun protection measures (see Directions), decreases the risk of skin cancer and early skin aging caused by the sun

Warnings

For external use only.

Do not use on

- damaged or broken skin.

When using this product

- keep out of eyes. Rinse with water to remove.

Stop use and ask a doctor

- if rash occurs.

Keep Out of Reach of Children

If swallowed, get medical help or contact a Poison Control Center right away.

Directions

- Apply liberally 15 minutes before sun exposure.
- Reapply at least every 2 hours.
- Use water-resistant sunscreen if swimming or sweating. Children under 6 months: ask a doctor.
- Sun Protection Measures: Spending time in the sun increases your risk of skin cancer and early skin aging. To decrease this risk regularly use a sunscreen with a Broad Spectrum SPF value of 15 or higher and other sun protection measures including:
  - limit time in the sun, especially from 10 a.m. - 2 p.m.
  - wear long-sleeved shirts, pants, hats and sunglasses.

Other Information

- protect the product in this container from excessive heat and direct sun

Inactive Ingredients

water, C12-15 alkyl benzoate, caprylic/capric triglyceride, potassium cetyl phosphate, cyclopentasiloxane, titanium dioxide, glyceryl myristate, isononyl isononanoate, talc, behenyl alcohol, glycerin, propylene glycol, microcrystalline cellulose, cellulose gum, mineral oil, phenoxyethanol, ethylhexylglycerin, nylon-12, fragance, ammonium acryloyldimethyltaurate/VP copolymer, triethanolamine, butylene glycol, allantoin, caffeine, ascorbyl glucoside, disodium EDTA, tocopheryl actetate, BHT, hyaluronic acid, iron oxides.

Questions or Comments

1-888-309-9030

Package/Label Principal Display Panel

DG™ beauty Skin Corrective BB Cream Broad Spectrum SPF15 Sunscreen

- For Light/Medium skin tones
- Renews
- Brightens
- Evens out
- Hydrates

Compare to Garnier® Skin Renew Miracle Skin Protector BB Cream SPF Ingredients*

2.5 FL OZ (75 mL)

*This product is not manufactured or distributed by Garnier®, owner of the registered trademark Skin Renew.

100% Quality Guaranteed (888) 309-9030

DISTRIBUTED BY DOLGENCORP, LLC
100 MISSION RIDGE
GOODLETTSVILLE, TN 37072
MANUFACTURED IN ISRAEL
6A418 VT C1

Carton Label